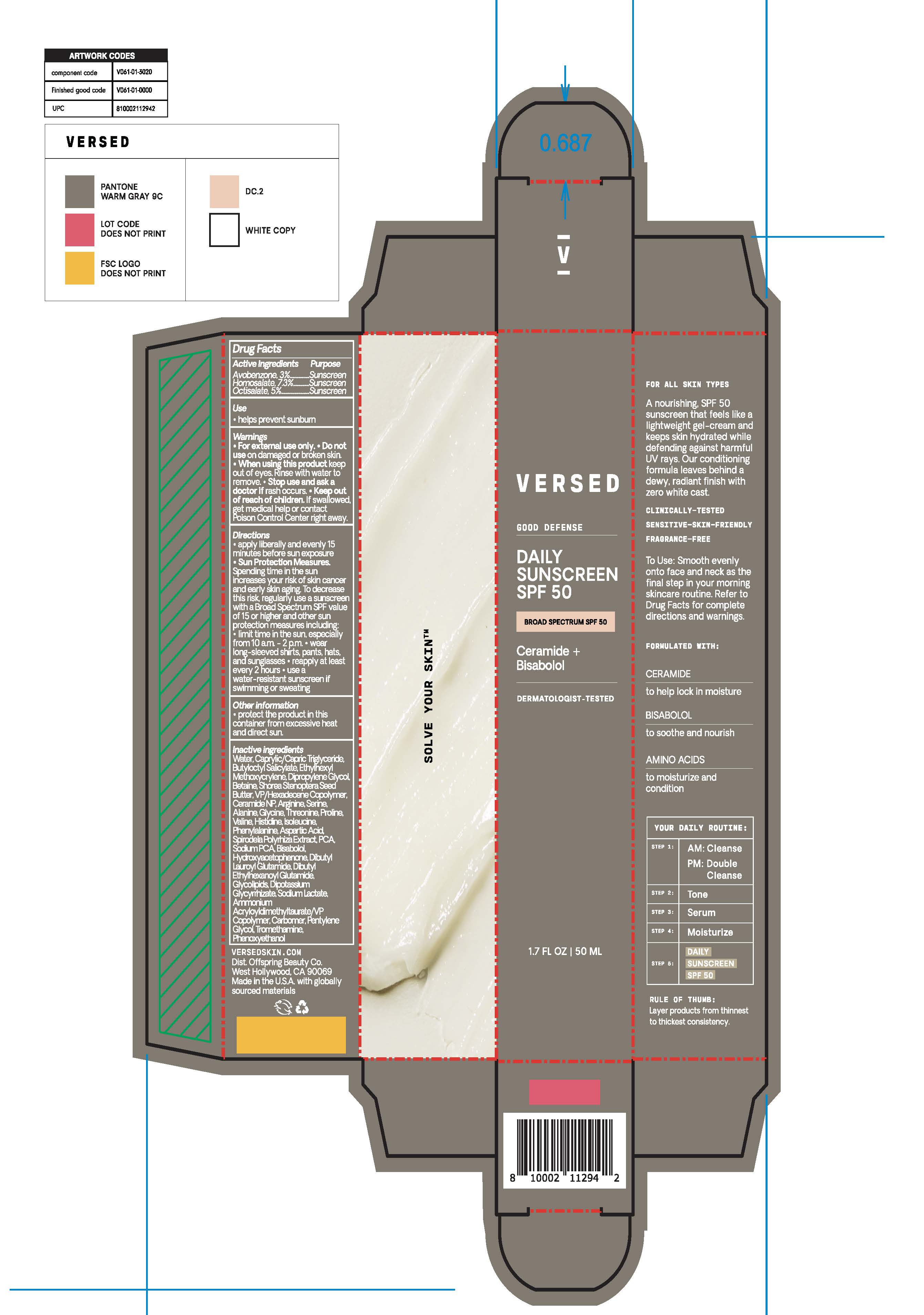 DRUG LABEL: Good Defense Daily Sunscreen
NDC: 73690-029 | Form: GEL
Manufacturer: Offspring Beauty Co.
Category: otc | Type: HUMAN OTC DRUG LABEL
Date: 20251023

ACTIVE INGREDIENTS: OCTISALATE 5 g/100 mL; AVOBENZONE 3 g/100 mL; HOMOSALATE 7.3 g/100 mL
INACTIVE INGREDIENTS: DIBUTYL ETHYLHEXANOYL GLUTAMIDE; VALINE; CAPRYLIC/CAPRIC TRIGLYCERIDE; SHOREA STENOPTERA SEED BUTTER; CERAMIDE NP; ISOLEUCINE; HYDROXYACETOPHENONE; ASPARTIC ACID; BISABOLOL; DIPROPYLENE GLYCOL; WATER; PHENYLALANINE; PENTYLENE GLYCOL; BUTYLOCTYL SALICYLATE; GLYCINE; THREONINE; TROMETHAMINE; HISTIDINE; DIPOTASSIUM GLYCYRRHIZATE; SODIUM LACTATE; PROLINE; SODIUM PCA; DIBUTYL LAUROYL GLUTAMIDE; ETHYLHEXYL METHOXYCRYLENE; SERINE; CARBOMER; VP/HEXADECENE COPOLYMER; ARGININE; BETAINE; ALANINE; AMMONIUM ACRYLOYLDIMETHYLTAURATE/VP COPOLYMER; PHENOXYETHANOL; SPIRODELA POLYRHIZA; PYRROLIDONE CARBOXYLIC ACID

Versed - Good Defense Daily Sunscreen SPF50

ACTIVE INGREDIENTS

Avobenzone 3%
Homosalate 7.3%
Octisalate 5%

PURPOSE

SUNSCREEN

USE

- HELPS PREVENT SUNBURN

WARNINGS

- FOR EXTERNAL USE ONLY.
- DO NOT USE ON DAMAGE OR BROKEN SKIN.
- WHEN USING THIS PRODUCT KEEP OUT OF EYES. RINSE WITH WATER TO REMOVE.

- KEEP OUT OF REACH OF CHILDREN. IF SWALLOWED, GET MEDICAL HELP OR CONTACT POISON CONTROL CENTER RIGHT AWAY.

- STOP USE AND ASK A DOCTOR IF RASH OCCURS.

DIRECTIONS

- APPLY LIBERALLY AND EVENLY 15 MINUTES BEFORE SUN EXPOSURE.
- REAPPLY AT LEAST EVERY 2 HOURS
- USE A WATER-RESISTANT SUNSCREEN IF SWIMMING OR SWEATING

OTHER SAFETY INFORMATION

SUN PROTECTION MEASURES: SPENDING TIME IN THE SUN INCREASES YOUR RISK OF SKIN CANCER AND EARLY SKIN AGING. TO DECREASE THIS RISK, REGULARLY USE A SUNSCREEN WITH A BROAD SPECTRUM SPF VALUE OF 15 OR HIGHER AND OTHER SUN PROTECTION MEASURES INCLUDING:

- LIMIT TIME IN THE SUN, ESPECIALLY FROM 10 A.M. - 2 P.M.
- WEAR LONG-SLEEVED SHIRTS, PANTS, HATS, AND SUNGLASSES

OTHER INFORMATION

- PROTECT THE PRODUCT IN THIS CONTAINER FROM EXCESSIVE HEAT AND DIRECT SUN.

INACTIVE INGREDIENTS

Water, Caprylic/Capric Triglyceride, Butyloctyl Salicylate, Ethylhexyl Methoxycrylene, Dipropylene Glycol, Betaine, Shorea Stenoptera Seed Butter, VP/Hexadecene Copolymer, Ceramide NP, Arginine, Serine, Alanine, Glycine, Threonine, Proline, Valine, Histidine, Isoleucine, Phenylalanine, Aspartic Acid, Spirodela Polyrhiza Extract, PCA, Sodium PCA, Bisabolol, Hydroxyacetophenone, Dibutyl Lauroyl Glutamide, Dibutyl Ethylhexanoyl Glutamide, Glycolipids, Dipotassium Glycyrrhizate, Sodium Lactate, Ammonium Acryloyldimethyltaurate/VP Copolymer, Carbomer, Pentylene Glycol, Tromethamine, Phenoxyethanol